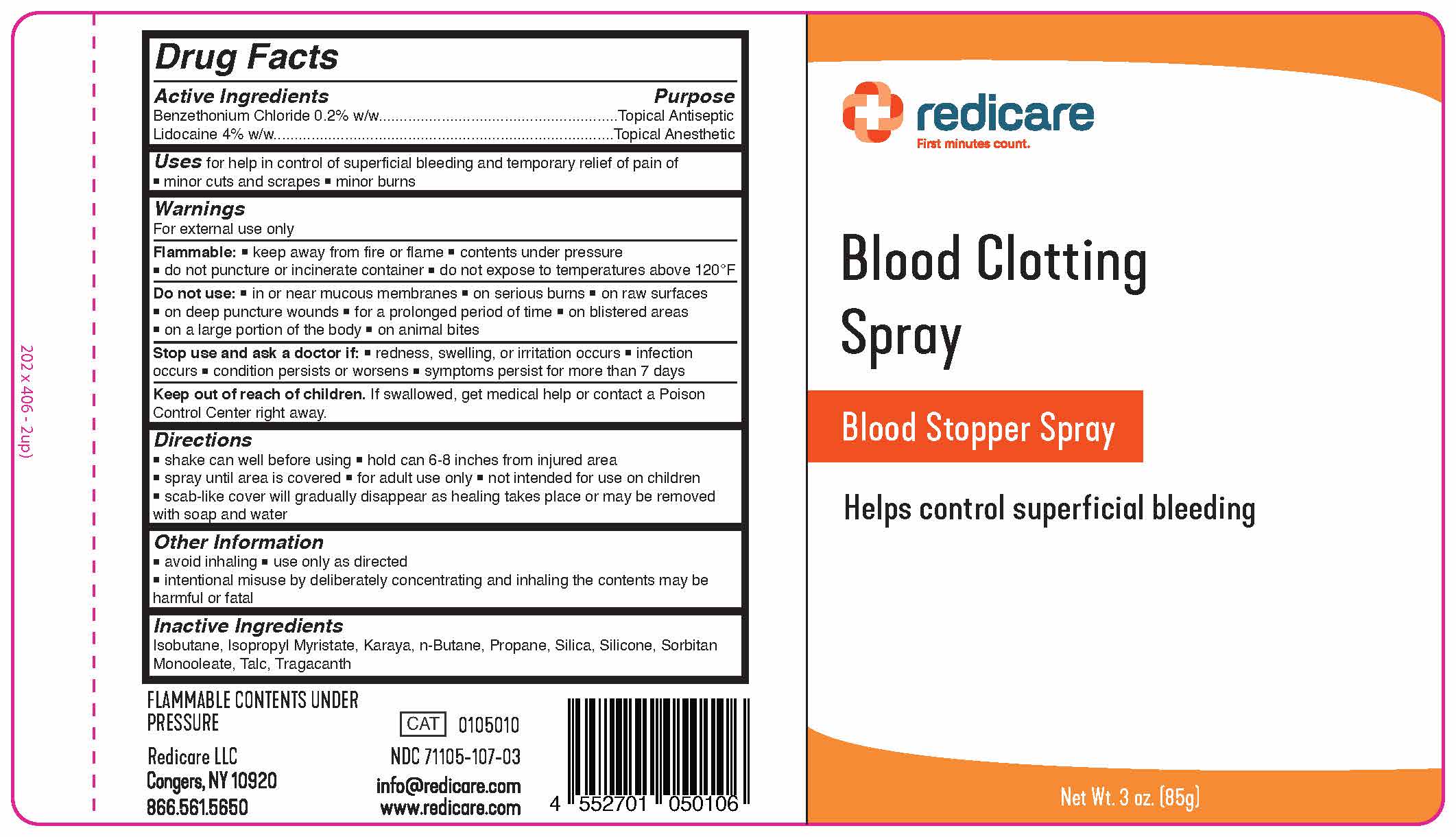 DRUG LABEL: Redicare Blood Clotting
NDC: 71105-107 | Form: AEROSOL, SPRAY
Manufacturer: Redicare LLC
Category: otc | Type: HUMAN OTC DRUG LABEL
Date: 20250825

ACTIVE INGREDIENTS: BENZETHONIUM CHLORIDE 170 mg/85 g; LIDOCAINE 3400 mg/85 g
INACTIVE INGREDIENTS: 3-(TRIETHOXYSILYL)PROPYLAMINE; ISOPROPYL MYRISTATE; PROPANE; TRAGACANTH; TALC; ISOBUTANE; BUTANE; SORBITAN MONOOLEATE; KARAYA GUM; SILICON DIOXIDE

Blood Clotting Spray

Active Ingredients

Benzethonium Chloride 0.2% w/w

Lidocaine 4% w/w

Purpose

Topical Antiseptic

Topical Antiseptic

Uses

- for help in the control of superficial bleeding
- for temporary relief of pain and to help protect against skin infection in minor cuts, minor scrapes, and minor burns

WARNINGS

For external use only.

Flammable

- Keep away from flame. Contents under pressure.
- Do not puncture or incinerate.
- Do not expose to temperatures above 120°(F)

DO NOT USE

- in eyes or other mucous membranes
- on large portions of the body
- in case of deep or puncture wounds
- on raw surfaces
- on blistered areas
- on animal bites
- on serious burns

DO NOT USE

- in eyes or other mucous membranes
- on large portions of the body
- in case of deep or puncture wounds
- on raw surfaces
- on blistered areas
- on animal bites
- on serious burns

Stop use and ask doctor if:

- Redness, swelling, or irritation occurs
- Infection occurs
- The condition persists or worsens
- Symptoms persist for more than 7 days

Stop use and ask doctor if:

- Redness, swelling, or irritation occurs
- Infection occurs
- The condition persists or worsens
- Symptoms persist for more than 7 days

Keep out of reach of children.

If swallowed, get medical help or contact a Poison Control Center right away.

Directions

- shake well before using
- hold 6-8 inches from moist injured area
- spray until the area is covered
- Scab-like cover will gradually disappear as healing takes place or may be removed with soap and water
- for adult institutional use only
- not intended for use on children

Inactive Ingredients

Isobutane, Isopropyl Myristate, Karaya, N-Butane, Propane, Silica, Silicone, Sorbitan Monooleate, Talc, Tragacanth